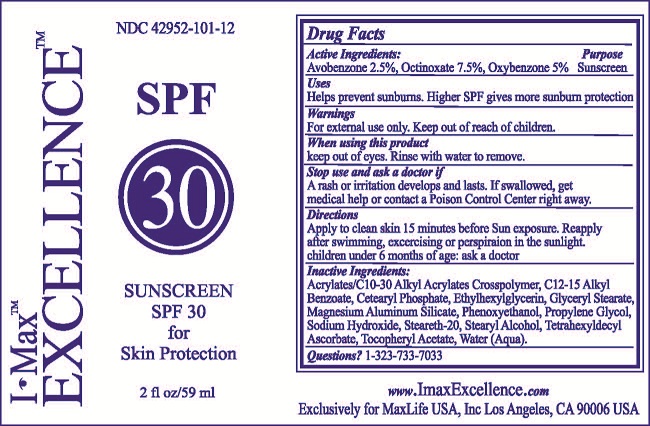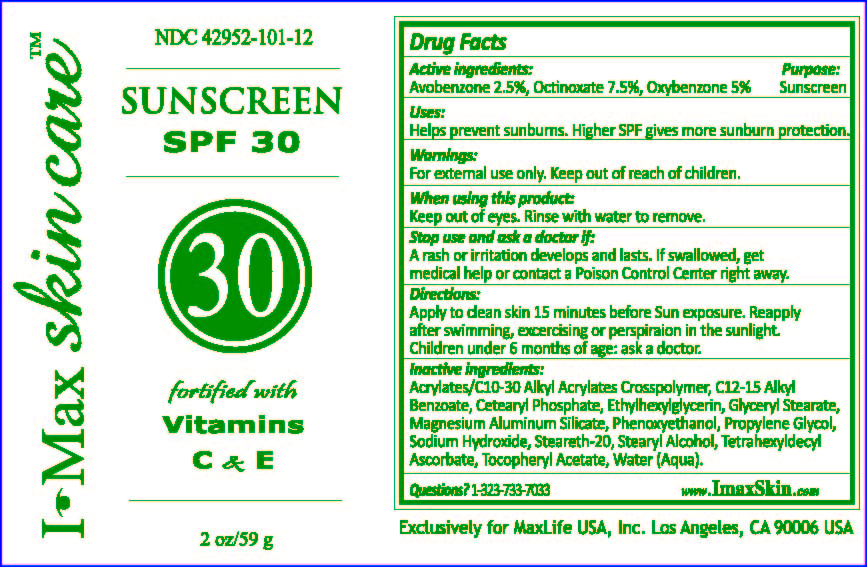 DRUG LABEL: I-MAX EXCELLENCE
NDC: 42952-101 | Form: LOTION
Manufacturer: MAXLIFE USA, INC.
Category: otc | Type: HUMAN OTC DRUG LABEL
Date: 20181107

ACTIVE INGREDIENTS: AVOBENZONE 2.5 g/100 mL; OCTINOXATE 7.5 g/100 mL; OXYBENZONE 5 g/100 mL
INACTIVE INGREDIENTS: ALKYL (C12-15) BENZOATE; CARBOMER INTERPOLYMER TYPE A (55000 CPS); GLYCERYL MONOSTEARATE; CETYL PHOSPHATE; ETHYLHEXYLGLYCERIN; MAGNESIUM ALUMINUM SILICATE; PHENOXYETHANOL; PROPYLENE GLYCOL; SODIUM HYDROXIDE; STEARETH-20; STEARYL ALCOHOL; TETRAHEXYLDECYL ASCORBATE; ALPHA-TOCOPHEROL ACETATE; WATER

ACTIVE INGREDIENTS:

AVOBENZONE 2.5%

OCTINOXATE 7.5%

OXYBENZONE 5%

PURPOSE:

SUNSCREEN

USES:

HELPS PREVENT SUNBURNS. HIGHER SPF GIVES MORE SUNBURN PROTECTION.

WARNINGS

FOR EXTERNAL USE ONLY.

KEEP OUT OF REACH OF CHILDREN.

WHEN USING THIS PRODUCT

KEEP OUT OF EYES. RINSE WITH WATER TO REMOVE.

STOP USE AND ASK A DOCTOR IF

A RASH OR IRRITATION DEVELOPS AND LASTS. IF SWALLOWED, GET

MEDICAL HELP OR CONTACT A POISON CONTROL CENTER RIGHT AWAY.

DIRECTIONS

APPLY TO CLEAN SKIN 15 MINUTES BEFORE SUN EXPOSURE. REAPPLY

AFTER SWIMMING, EXCERCISING OR PERSPIRATION IN THE SUNLIGHT.

CHILDREN UNDER 6 MONTHS OF AGE: ASK A DOCTOR.

INACTIVE INGREDIENTS:

ALKYL BENZOATE, ACRYLATES/C10-30 ALKYL ACRYLATES CROSSPOLYMER, C12-15 GLYCERYL STEARATE, CETEARYL PHOSPHATE, ETHYLHEXYLGLYCERIN, MAGNESIUM ALUMINUM SILICATE, PHENOXYETHANOL, PROPYLENE GLYCOL, SODIUM HYDROXIDE, STEARETH-20, STEARYL ALCOHOL, TETRAHEXYLDECYL ASCORBATE, TOCOPHERYL ACETATE, WATER (AQUA).

QUESTIONS? 1-323-733-7033